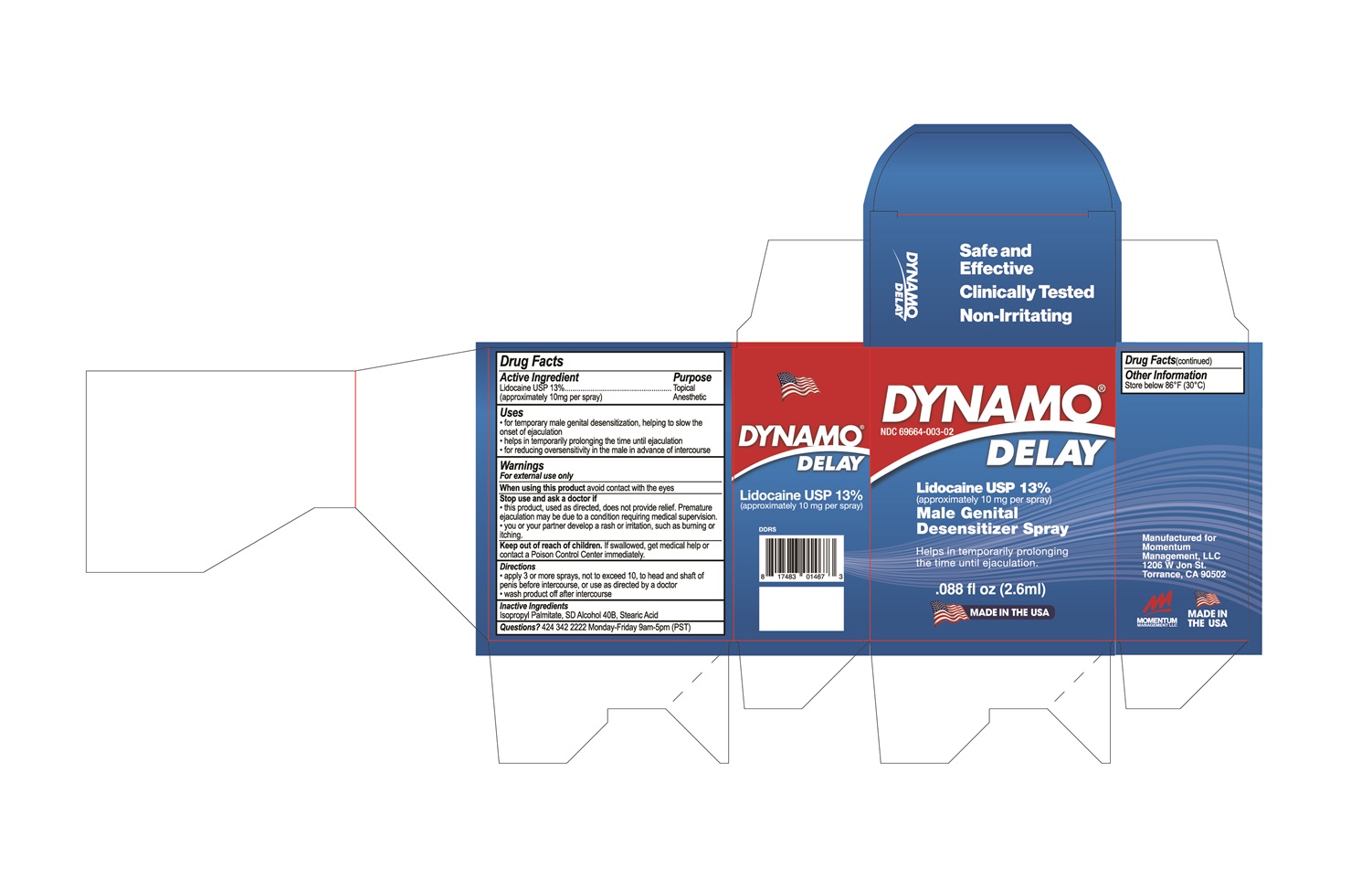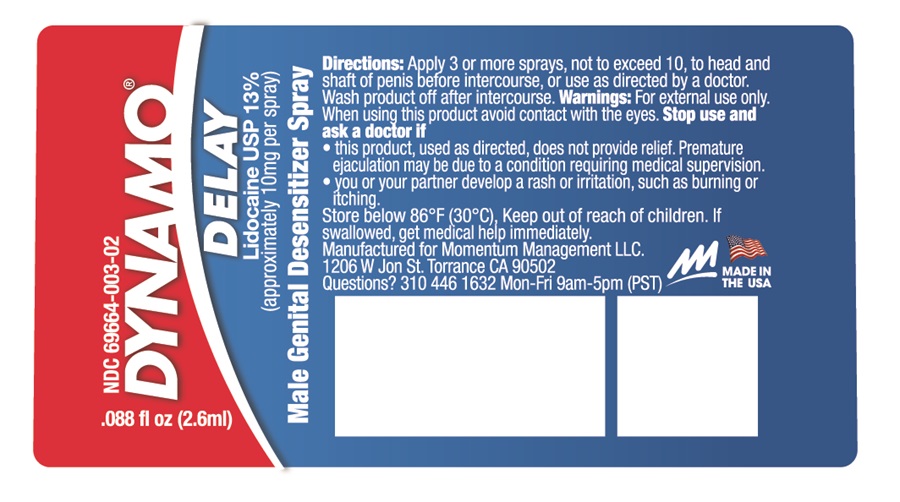 DRUG LABEL: DYNAMO DELAY SAMPLE BOTTLE
NDC: 69664-003 | Form: SPRAY
Manufacturer: Momentum Management LLC
Category: otc | Type: Human OTC Drug Label
Date: 20260119

ACTIVE INGREDIENTS: LIDOCAINE 10 mg/0.08 mL
INACTIVE INGREDIENTS: ISOPROPYL PALMITATE; ALCOHOL; STEARIC ACID

BU05-Delay Spray For Men

ACTIVE INGREDIENT

Lidocaine USP 13%
(approximately 10 mg per spray)

PURPOSE

Topical Anesthetic

USE(S)

- for temporary male genital desensitization, helping to slow the onset of ejaculation
- helps in temporarily prolonging the time until ejaculation
- for reducing oversensitivity in the male in advance of intercourse

WARNINGS

For external use only

WHEN USING THIS PRODUCT

avoid contact with the eyes

STOP USE AND ASK A DOCTOR IF

- this product, used as directed, does not provide relief. Premature ejaculation may be due to a condition requiring medical supervision.
- you or your partner develop a rash or irritation, such as burning or itching.

KEEP OUT OF REACH OF CHILDREN

If swallowed, get medical help or contact a Poison Control Center immediately

DIRECTIONS

- apply 3 or more sprays, not to exceed 10, to head and shaft of penis before intercourse, or use as directed by a doctor.
- wash product off after intercourse

INACTIVE INGREDIENTS

Isopropyl Palmitate, SD Alcohol 40B, Stearic Acid

QUESTIONS?

310 446 1632 Monday - Friday 9am-5pm(PST)
Manufactured for
Momentum Management LLC
1206 W Jon St
Torrance, CA 90502

PRINCIPAL DISPLAY PANEL

Dynamo Delay
NDC 69664-003-02
Lidocaine USP 13%
(approximately 10 mg per spray)
Male Genital Desensitizer Spray
Helps in temporarily prolonging the time until ejaculation.
.088 fl oz (2.6mL)
Made in the USA